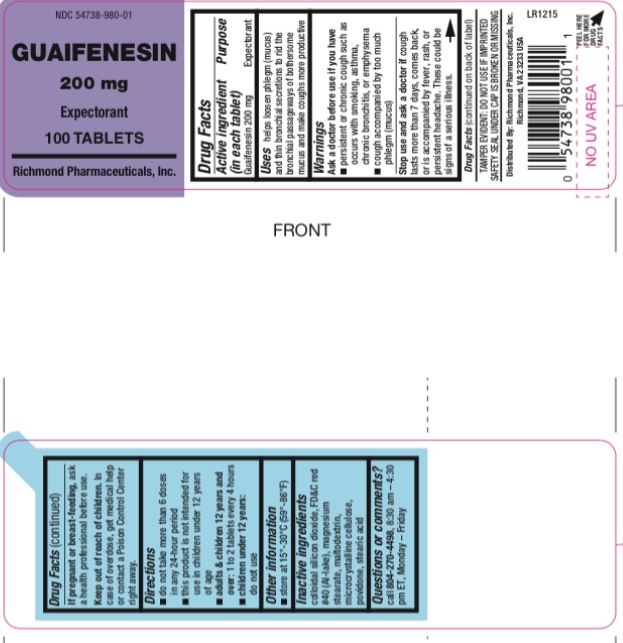 DRUG LABEL: Mucus Relief
NDC: 54738-980 | Form: TABLET
Manufacturer: Richmond Pharmaceuticals, Inc.
Category: otc | Type: HUMAN OTC DRUG LABEL
Date: 20180813

ACTIVE INGREDIENTS: GUAIFENESIN 200 mg/1 1
INACTIVE INGREDIENTS: FD&C RED NO. 40; SILICON DIOXIDE; MAGNESIUM STEARATE; CELLULOSE, MICROCRYSTALLINE; MALTODEXTRIN; POVIDONE; STEARIC ACID

Guaifenesin Caplets, 200 mg

Active ingredient (in each tablet)

Guaifenesin 200 mg

Purpose

Expectorant

Uses

- helps loosen phlegm (mucus) and thin bronchial secretions to make coughs more productive to rid the bronchial passageway of bothersome mucus and make cough more productive

Warnings

ask a doctor before use if you have

- persistent or chronic cough such as occurs with smoking, asthma, chronic bronchitis or emphysema
- cough accompanied by excessive phlegm (mucus)

KEEP OUT OF REACH OF CHILDREN

In case of overdose, get medical help or contact a Poison Control Center right away.

IN CASE OF PREGNANCY OR BREAST FEEDING SECTION

ask a health professional before use

stop use and ask a doctor

if cough lasts more than 7 days, comes back, or is accompanied by fever, rash or persistent headache.These could be signs of serious illness

Directions:

- adults and children 12 years of age and over: take 1 to 2 tablets every 4 hours with a full glass of water while symptoms persist. Do not exceed 6 doses in 24 hours.
- children under 12 years: do not use

OTHER INFORMATION

- store at 15°-30°C (59°-86°F)
- TAMPER EVIDENT: DO NOT USE IF IMPRINTED SAFETY SEAL UNDER CAP IS BROKEN OR MISSING

Inactive ingredients

colloidal silicon dioxide, FD&C RED#40(Al-lake), magnesium stearate, maltodextrin, microcrystalline cellulose, stearic acid, sodium starch glycolate

Questions or Comments

call 804-270-4498, 8.30 am-4.30 pm ET, Monday - Friday
TAMPER EVIDENT: DO NOT USE IF IMPRINTED SAFETY SEAL UNDER CAP IS BROKEN OR MISSING

PACKAGE LABEL

Guaifenesin 200 mg...Expectorant
NDC- 54738-980-01... 100 CAPLETS